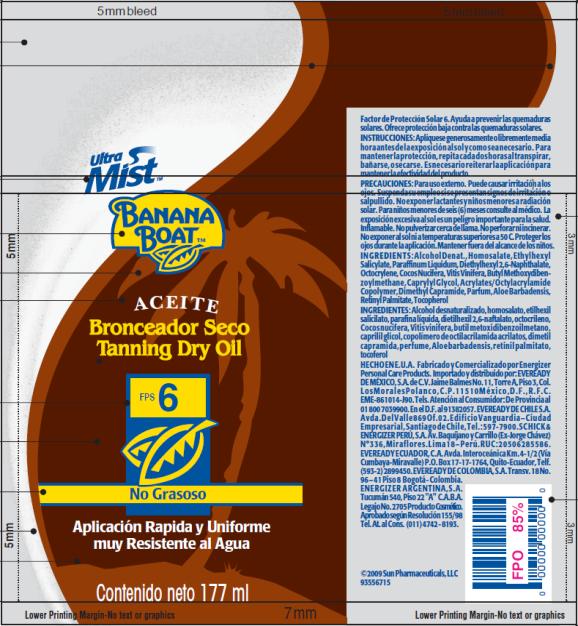 DRUG LABEL: Banana Boat Aceite Bronceador Seco Tanning Dry SPF 6
NDC: 17630-2025 | Form: OIL
Manufacturer: Accra-Pac, Inc.
Category: otc | Type: HUMAN OTC DRUG LABEL
Date: 20100318

ACTIVE INGREDIENTS: HOMOSALATE 0.04 mL/1 mL; OCTISALATE 0.04 mL/1 mL; OCTOCRYLENE 0.025 mL/1 mL; AVOBENZONE 0.01 mL/1 mL
INACTIVE INGREDIENTS: MINERAL OIL; CAPRYLYL GLYCOL; VITAMIN A PALMITATE; ALOE VERA LEAF; GRAPE SEED OIL; COCONUT OIL

Banana Boat Aceite Bronceador Seco Tanning Dry Oil SPF 6

Active Ingredients:

Homosalate 0.04mL / 1mL

Octisalate 0.04mL / 1mL

Octocrylene 0.025mL / 1mL

Avobenzone 0.01mL / 1mL

INSTRUCCIONES:

Aplíquese generosamente o libremente media hora antes de la exposición al sol y como sea necesario. Para mantener la protección, repita cada dos horas al transpirar, bañarse, o secarse. Es necesario reiterar la aplicación para mantener la efectividad del producto.

PRECAUCIONES:

Para uso externo. Puede causar irritación a los ojos. Suspenda su empleo si se presentan signos de irritación o salpullido. No exponer lactantes y niños menores a radiación solar. Para niños menores de seis (6) meses consulte al médico. La exposición excesiva al sol es un peligro importante para la salud. Inflamable. No pulverizar cerca de llama. No perforar ni incinerar. No exponer al sol ni a temperaturas superiores a 50 C. Proteger los ojos durante la aplicación. Mantener fuera del alcance de los niños.

INGREDIENTS:

Alcohol Denat., Homosalate, Ethylhexyl Salicylate, Paraffinum Liquidum, Diethylhexyl 2,6-Naphthalate, Octocrylene, Cocos Nucifera, Vitis Vinifera, Butyl Methoxydibenzoylmethane, Caprylyl Glycol, Acrylates/Octylacrylamide Copolymer, Dimethyl Capramide, Parfum, Aloe Barbadensis, Retinyl Palmitate, Tocopherol

INGREDIENTES:

Alcohol desnaturalizado, homosalato, etilhexil salicilato, parafina líquida, dietilhexil 2,6-naftalato, octocrileno, Cocos nucifera, Vitis vinifera, butil metoxidibenzoilmetano, caprilil glicol, copolímero de octilacrilamida acrilatos, dimetil capramida, perfume, Aloe barbadensis, retinil palmitato, tocoferol

HECHO EN E.U.A. Fabricado y Comercializado por Energizer Personal Care Products. Importado y distribuido por: EVEREADY DE MÉXICO, S.A. de C.V. Jaime Balmes No. 11, Torre A, Piso 3, Col. Los Morales Polanco, C.P. 11510 México, D.F., R.F.C. EME-861014-J90. Tels. Atención al Consumidor: De Provincia al 01 800 7039900. En el D.F. al 91382057. EVEREADY DE CHILE S.A. Avda. Del Valle 869 Of.02. Edificio Vanguardia – Ciudad Empresarial, Santiago de Chile, Tel.: 597-7900. SCHICK & ENERGIZER PERÚ, S.A. Av. Baquíjano y Carrillo (Ex-Jorge Chávez) N° 336, Miraflores. Lima 18 – Perú. RUC: 20506285586. EVEREADY ECUADOR, C.A. Avda. Interoceánica Km. 4-1/2 (Vía Cumbaya-Miravalle) P.O. Box 17-17-1764, Quito-Ecuador, Telf. (593-2) 2899450. EVEREADY DE COLOMBIA, S.A. Transv. 18 No. 96 – 41 Piso 8 Bogotá - Colombia. ENERGIZER ARGENTINA, S.A. Tucumán 540, Piso 22 "A" C.A.B.A. Legajo No. 2705 Producto Cosmético. Aprobado según Resolución 155/98 Tel. At. al Cons. (011) 4742 - 8193.

PRINCIPAL DISPLAY PANEL

UltraMist TM
Banana Boat TM
Aceite
Bronceador Seco
Tanning Dry Oil
FPS 6
No Grasoso
Aplicación Rapida y Uniforme
muy Resistente al Agua
Contenido neto 177 ml